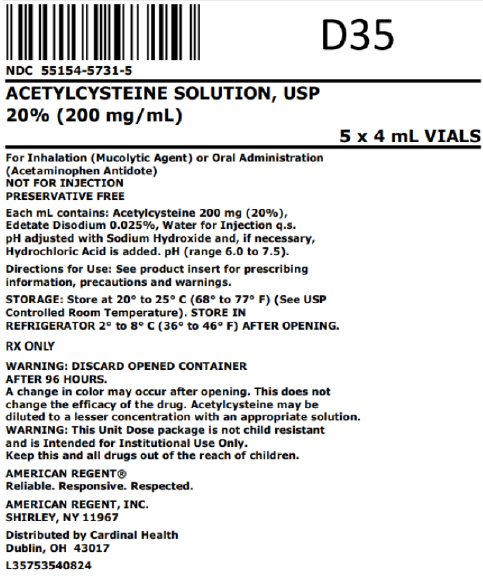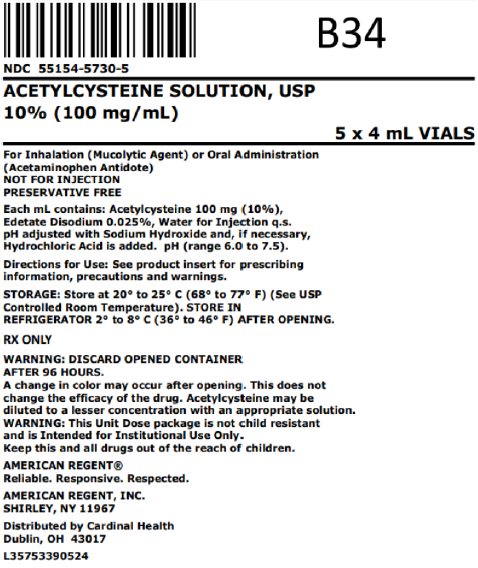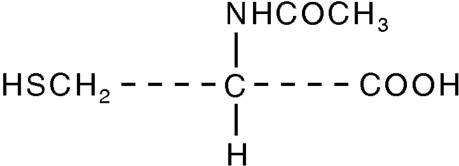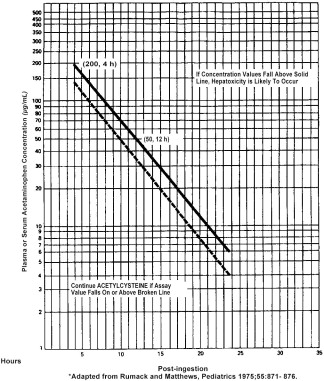 DRUG LABEL: Acetylcysteine
NDC: 55154-5730 | Form: INHALANT
Manufacturer: Cardinal Health 107, LLC
Category: prescription | Type: HUMAN PRESCRIPTION DRUG LABEL
Date: 20250923

ACTIVE INGREDIENTS: ACETYLCYSTEINE 100 mg/1 mL
INACTIVE INGREDIENTS: EDETATE DISODIUM; WATER

Acetylcysteine Solution, USP

Sterile
Not For Injection

DESCRIPTION

Acetylcysteine is for inhalation (mucolytic agent) or oral administration (acetaminophen antidote), available as a sterile, unpreserved solution (NOT FOR INJECTION). The solutions contain 20% (200 mg/mL) or 10% (100 mg/mL) acetylcysteine, with disodium edetate in water for injection. Sodium hydroxide and/or hydrochloric acid is added to adjust pH (range 6.0 - 7.5). Acetylcysteine is the N-acetyl derivative of the naturally-occurring amino acid, L-cysteine. The compound is a white crystalline powder with the molecular formula C5H9NO3S, a molecular weight of 163.2, and chemical name of N-acetyl-L-cysteine. Acetylcysteine has the following structural formula:

This product contains the following inactive ingredients:
disodium edetate, sodium hydroxide and water for injection.

CLINICAL PHARMACOLOGY

The viscosity of pulmonary mucous secretions depends on the concentrations of mucoprotein and, to a lesser extent, deoxyribonucleic acid (DNA). The latter increases with increasing purulence owing to the presence of cellular debris. The mucolytic action of acetylcysteine is related to the sulfhydryl group in the molecule. This group probably ``opens′′ disulfide linkages in mucus thereby lowering the viscosity. The mucolytic activity of acetylcysteine is unaltered by the presence of DNA, and increases with increasing pH. Significant mucolysis occurs between pH 7 and 9.

Acetylcysteine undergoes rapid deacetylation in vivo to yield cysteine or oxidation to yield diacetylcystine.

Occasionally, patients exposed to the inhalation of an acetylcysteine aerosol respond with the development of increased airways obstruction of varying and unpredictable severity. Those patients who are reactors cannot be identified a priori from a random patient population. Even when patients are known to have reacted previously to the inhalation of an acetylcysteine aerosol, they may not react during a subsequent treatment. The converse is also true; patients who have had inhalation treatments of acetylcysteine without incident may still react to subsequent inhalation with increased airways obstruction. Most patients with bronchospasm are quickly relieved by the use of a bronchodilator given by nebulization. If bronchospasm progresses, the medication should be discontinued immediately.

INDICATIONS AND USAGE

Acetylcysteine is indicated as adjuvant therapy for patients with abnormal, viscid, or inspissated mucous secretions in such conditions as:

Chronic bronchopulmonary disease (chronic emphysema, emphysema with bronchitis, chronic asthmatic bronchitis, tuberculosis, bronchiectasis and primary amyloidosis of the lung)
Acute bronchopulmonary disease (pneumonia, bronchitis, tracheobronchitis)
Pulmonary complications of cystic fibrosis
Tracheostomy care
Pulmonary complications associated with surgery
Use during anesthesia
Post-traumatic chest conditions
Atelectasis due to mucous obstruction
Diagnostic bronchial studies (bronchograms, bronchospirometry, and bronchial wedge catheterization)

CONTRAINDICATIONS

Acetylcysteine is contraindicated in those patients who are sensitive to it.

WARNINGS

After proper administration of acetylcysteine, an increased volume of liquified bronchial secretions may occur. When cough is inadequate, the open airway must be maintained open by mechanical suction if necessary. When there is a mechanical block due to foreign body or local accumulation, the airway should be cleared by endotracheal aspiration, with or without bronchoscopy. Asthmatics under treatment with acetylcysteine should be watched carefully. Most patients with bronchospasm are quickly relieved by the use of a bronchodilator given by nebulization. If bronchospasm progresses, the medication should be discontinued immediately.

PRECAUTIONS

General

With the administration of acetylcysteine, the patient may initially observe a slight disagreeable odor that is soon not noticeable. With a face mask there may be stickiness on the face after nebulization. This is easily removed by washing with water.

Under certain conditions, a color change may occur in the opened bottle of acetylcysteine. The light purple color is the result of a chemical reaction which does not significantly affect the safety or mucolytic effectiveness of acetylcysteine.

Continued nebulization of acetylcysteine solution with a dry gas will result in an increased concentration of the drug in the nebulizer because of evaporation of the solvent. Extreme concentration may impede nebulization and efficient delivery of the drug. Dilution of the nebulizing solution with appropriate amounts of Sterile Water for Injection, USP, as concentration occurs, will obviate this problem.

Drug Interactions

Drug stability and safety of acetylcysteine when mixed with other drugs in a nebulizer have not been established.

Carcinogenesis, Mutagenesis, Impairment of Fertility:

Carcinogenesis

Carcinogenicity studies in laboratory animals have not been performed with acetylcysteine alone, nor with acetylcysteine in combination with isoproterenol.

Long-term oral studies of acetylcysteine alone in rats (12 months of treatment followed by 6 months of observation) at doses up to 1,000 mg/kg/day (5.2 times the human mucolytic dose) provided no evidence of oncogenic activity.

Mutagenesis

Published data^1 indicate that acetylcysteine is not mutagenic in the Ames test, both with and without metabolic activation.

Impairment of Fertility

A reproductive toxicity test to assess potential impairment of fertility was performed with acetylcysteine (10%) combined with isoproterenol (0.05%) and administered as an aerosol into a chamber of 12.43 cubic meters. The combination was administered for 25, 30, or 35 minutes twice a day for 68 days before mating, to 200 male and 150 female rats; no adverse effects were noted in dams or pups. Females after mating were continued on treatment for the next 42 days.

Reproductive toxicity studies of acetylcysteine in the rat given oral doses of acetylcysteine up to 1,000 mg/kg (5.2 times the human mucolytic dose) have also been reported in the literature.^1 The only adverse effect observed was a slight non-dose-related reduction in fertility at dose levels of 500 or 1,000 mg/kg/day (2.6 or 5.2 times the human mucolytic dose) in the Segment I study.

Pregnancy: Teratogenic Effects: Pregnancy Category B

In a teratology study of acetylcysteine in the rabbit, oral doses of 500 mg/kg/day (2.6 times the human mucolytic dose) were administered to pregnant does by intubation on days 6 through 16 of gestation. Acetylcysteine was found to be nonteratogenic under the conditions of the study.

In the rabbit, two groups (one of 14 and one of 16 pregnant females) were exposed to an aerosol of 10% acetylcysteine and 0.05% isoproterenol hydrochloride for 30 and 35 minutes twice a day from the 6th through the 18th day of pregnancy. No teratogenic effects were observed among the offspring.

Teratology and a perinatal or postnatal toxicity study in rats were performed with a combination of acetylcysteine and isoproterenol administered by the inhalation route. In the rat, two groups of 25 pregnant females each were exposed to the aerosol for 30 and 35 minutes, respectively, twice a day from the 6th through the 15th day of gestation. No teratogenic effects were observed among the offspring.

In the pregnant rat (30 rats per group), twice-daily exposure to an aerosol of acetylcysteine and isoproterenol for 30 or 35 minutes from the 15th day of gestation through the 21st day postpartum was without adverse effect on dams or newborns.

Reproduction studies of acetylcysteine with isoproterenol have been performed in rats and of acetylcysteine alone in rabbits at doses up to 2.6 times the human dose. These have revealed no evidence of impaired fertility or harm to the fetus due to acetylcysteine. There are, however, no adequate and well-controlled studies in pregnant women. Because animal reproduction studies may not always be predictive of human responses, this drug should be used during pregnancy only if clearly needed.

Nursing Mothers

It is not known whether this drug is excreted in human milk. Because many drugs are excreted in human milk, caution should be exercised when acetylcysteine is administered to a nursing woman.

ADVERSE REACTIONS

Adverse effects have included stomatitis, nausea, vomiting, fever, rhinorrhea, drowsiness, clamminess, chest tightness, and bronchoconstriction. Clinically overt acetylcysteine induced bronchospasm occurs infrequently and unpredictably even in patients with asthmatic bronchitis or bronchitis complicating bronchial asthma.

Acquired sensitization to acetylcysteine has been reported rarely. Reports of sensitization in patients have not been confirmed by patch testing. Sensitization has been confirmed in several inhalation therapists who reported a history of dermal eruptions after frequent and extended exposure to acetylcysteine.

Reports of irritation to the tracheal and bronchial tracts have been received and although hemoptysis has occurred in patients receiving acetylcysteine such findings are not uncommon in patients with bronchopulmonary disease and a causal relationship has not been established.

DOSAGE AND ADMINISTRATION

General

Acetylcysteine is available in rubber stoppered glass vials containing 4, 10, or 30 mL. The 20% solution may be diluted to a lesser concentration with either Sodium Chloride Injection, Sodium Chloride Inhalation Solution, Sterile Water for Injection, or Sterile Water for Inhalation. The 10% solution may be used undiluted.

Acetylcysteine does not contain an antimicrobial agent, and care must be taken to minimize contamination of the sterile solution. If only a portion of the solution in a vial is used for inhalation, store the remainder in a refrigerator and use within 96 hours.

Nebulization-face mask, mouth piece, tracheostomy

When nebulized into a face mask, mouth piece, or tracheostomy, 1 to 10 mL of the 20% solution or 2 to 20 mL of the 10% solution may be given every 2 to 6 hours; the recommended dose for most patients is 3 to 5 mL of the 20% solution or 6 to 10 mL of the 10% solution 3 to 4 times a day.

Nebulization tent, Croupette

In special circumstances it may be necessary to nebulize into a tent or Croupette, and this method of use must be individualized to take into account the available equipment and the patient's particular needs. This form of administration requires very large volumes of the solution, occasionally as much as 300 mL during a single treatment period.

If a tent or Croupette must be used, the recommended dose is the volume of acetylcysteine (using 10% or 20%) that will maintain a very heavy mist in the tent or Croupette for the desired period. Administration for intermittent or continuous prolonged periods, including overnight, may be desirable.

Direct Instillation

When used by direct instillation, 1 to 2 mL of a 10% to 20% solution may be given as often as every hour.

When used for the routine nursing care of patients with tracheostomy, 1 to 2 mL of a 10% to 20% solution may be given every 1 to 4 hours by instillation into the tracheostomy.

Acetylcysteine may be introduced directly into a particular segment of the bronchopulmonary tree by inserting (under local anesthesia and direct vision) a small plastic catheter into the trachea. Two to 5 mL of the 20% solution may then be instilled by means of a syringe connected to the catheter.

Acetylcysteine may also be given through a percutaneous intratracheal catheter. One to 2 mL of the 20% or 2 to 4 mL of the 10% solution every 1 to 4 hours may then be given by a syringe attached to the catheter.

Diagnostic Bronchograms

For diagnostic bronchial studies, two or three administrations of 1 to 2 mL of the 20% solution or 2 to 4 mL of the 10% solution should be given by nebulization or by instillation intratracheally, prior to the procedure.

Administration of Aerosol

Materials

Acetylcysteine may be administered using conventional nebulizers made of plastic or glass. Certain materials used in nebulization equipment react with acetylcysteine. The most reactive of these are certain metals (notably iron and copper) and rubber. Where materials may come into contact with acetylcysteine solution, parts made of the following acceptable materials should be used: glass, plastic, aluminum, anodized aluminum, chromed metal, tantalum, sterling silver, or stainless steel. Silver may become tarnished after exposure, but this is not harmful to the drug action or to the patient.

Nebulizing Gases

Compressed tank gas (air) or an air compressor should be used to provide pressure for nebulizing the solution. Oxygen may also be used but should be used with the usual precautions in patients with severe respiratory disease and CO2 retention.

Apparatus

Acetylcysteine is usually administered as fine nebulae and the nebulizer used should be capable of providing optimal quantities of a suitable range of particle sizes.

Commercially available nebulizers will produce nebulae of acetylcysteine satisfactory for retention in the respiratory tract. Most of the nebulizers tested will supply a high proportion of the drug solution as particles of less than 10 microns in diameter. Mitchell^2 has shown that particles less than 10 microns should be retained in the respiratory tract satisfactorily.

Various intermittent positive pressure breathing devices nebulized acetylcysteine with a satisfactory efficiency including: No. 40 De Vilbiss (The De Vilbiss Co., Somerset, Pennsylvania), and the Bennett Twin-Jet Nebulizer (Puritan Bennett Corp., Oak at 13th., Kansas City, Missouri).

The nebulized solution may be inhaled directly from the nebulizer. Nebulizers may also be attached to the plastic face masks or plastic mouthpieces. Suitable nebulizers may also be fitted for use with the various intermittent positive pressure breathing (IPPB) machines. The nebulizing equipment should be cleaned immediately after use because the residues may clog the smaller orifices or corrode metal parts.

Hand bulbs are not recommended for routine use in nebulizing acetylcysteine because their output is generally too small. Also, some hand-operated nebulizers deliver particles that are larger than optimum for inhalation therapy.

Acetylcysteine should not be placed directly into the chamber of a heated (hot pot) nebulizer. A heated nebulizer may be part of the nebulization assembly to provide a warm saturated atmosphere if the acetylcysteine aerosol is introduced by means of a separate unheated nebulizer. Usual precautions for administration of warm saturated nebulae should be observed.

The nebulized solution may be breathed directly from the nebulizer. Nebulizers may also be attached to plastic face masks, plastic face tents, plastic mouth pieces, conventional plastic oxygen tents, or head tents. Suitable nebulizers may also be fitted for use with the various intermittent positive pressure breathing (IPPB) machines.

The nebulizing equipment should be cleaned immediately after use, otherwise the residues may occlude the fine orifices or corrode metal parts.

Prolonged Nebulization

When three fourths of the initial volume of acetylcysteine solution has been nebulized, a quantity of Sterile Water for Injection, USP (approximately equal to the volume of solution remaining) should be added to the nebulizer. This obviates any concentration of the agent in the residual solvent remaining after prolonged nebulization.

Compatibility

The physical and chemical compatibility of acetylcysteine solutions with certain other drugs that might be concomitantly administered by nebulization, direct instillation, or topical application has been studied.

Acetylcysteine should not be mixed with certain antibiotics. For example, the antibiotics, tetracycline hydrochloride, oxytetracycline hydrochloride, and erythromycin lactobionate, were found to be incompatible when mixed in the same solution. These agents may be administered from separate solutions if administration of these agents is desirable.

The supplying of these data should not be interpreted as a recommendation for combining acetylcysteine with other drugs. The table is not presented as positive assurance that no incompatibility will be present, since these data are based only on short-term compatibility studies done in the Mead Johnson Research Center. Manufacturers may change their formulations, and this could alter compatibilities. These data are intended to serve only as a guide for predicting compounding problems.

If it is deemed advisable to prepare an admixture, it should be administered as soon as possible after preparation. Do not store unused mixtures.

IN VITRO COMPATIBILITY^1 TESTS OF ACETYLCYSTEINE
 |  | RATIO TESTED^6
PRODUCT AND/OR AGENT | COMPATIBILITY | ACETYLCYSTEINE | PRODUCT
 | RATING |  | OR AGENT
ANESTHETIC, GAS
Halothane | Compatible | 20% | Infinite
Nitrous Oxide | Compatible | 20% | Infinite
ANESTHETIC, LOCAL
Cocaine HCl | Compatible | 10% | 5%
Lidocaine HCl | Compatible | 10% | 2%
Tetracaine HCl | Compatible | 10% | 1%
ANTIBACTERIALS (A parenteral form of each antibiotic was used)
Bacitracin^2,3 (mix and use at once) | Compatible | 10% | 5,000 U/mL
Chloramphenicol Sodium Succinate | Compatible | 20% | 20 mg/mL
Carbenicillin Disodium^2 (mix and use at once) | Compatible | 10% | 125 mg/mL
Gentamicin Sulfate^2 | Compatible | 10% | 20 mg/mL
Kanamycin Sulfate^2 (mix and use at once) | Compatible | 10% | 167 mg/mL
 | Compatible | 17% | 85 mg/mL
Lincomycin HCl^2 | Compatible | 10% | 150 mg/mL
Neomycin Sulfate^2 | Compatible | 10% | 100 mg/mL
Novobiocin Sodium^2 | Compatible | 10% | 25 mg/mL
Penicillin G Potassium^2 (mix and use at once) | Compatible | 10% | 25,000 U/mL
 | Compatible | 10% | 100,000 U/mL
Polymyxin B Sulfate^2 | Compatible | 10% | 50,000 U/mL
Cephalothin Sodium | Compatible | 10% | 110 mg/mL
Colistimethate Sodium^2 (mix and use at once) | Compatible | 10% | 37.5 mg/mL
Vancomycin HCl^2 | Compatible | 10% | 25 mg/mL
Amphotericin B | Incompatible | 4% - 15% | 1 - 4 mg/mL
Chlortetracycline HCl^2 | Incompatible | 10% | 12.5 mg/mL
Erythromycin Lactobionate | Incompatible | 10% | 15 mg/mL
Oxytetracycline HCl | Incompatible | 10% | 12.5 mg/mL
Ampicillin Sodium | Incompatible | 10% | 50 mg/mL
Tetracycline HCl | Incompatible | 10% | 12.5 mg/mL
BRONCHODILATORS
Isoproterenol HCl^2 | Compatible | 3% | 0.5%
Isoproterenol HCl^2 | Compatible | 10% | 0.05%
Isoproterenol HCl^2 | Compatible | 20% | 0.05%
Isoproterenol HCl | Compatible | 13.3% (2 parts) | 0.33% (1 part)
Isoetharine HCl | Compatible | 13.3% (2 parts) | (1 part)
Epinephrine HCl | Compatible | 13.3% (2 parts) | 0.33% (1 part)
CONTRAST MEDIA
Iodized Oil | Incompatible | 20%/20 mL | 40%/10 mL
DECONGESTANTS
Phenylephrine HCl^2 | Compatible | 3% | 0.25%
Phenylephrine HCl | Compatible | 13.3% (2 parts) | 0.17% (1 part)
ENZYMES
Chymotrypsin | Incompatible | 5% | 400 γ/mL
Trypsin | Incompatible | 5% | 400 γ/mL
SOLVENTS
Alcohol | Compatible | 12% | 10% - 20%
Propylene Glycol | Compatible | 3% | 10%
STEROIDS
Dexamethasone Sodium Phosphate | Compatible | 16% | 0.8 mg/mL
Prednisolone Sodium Phosphate^5 | Compatible | 16.7% | 3.3 mg/mL
OTHER AGENTS
Hydrogen Peroxide | Incompatible | (All ratios)
Sodium Bicarbonate | Compatible | 20% (1 part) | 4.2% (1 part)
1. The rating, Incompatible, is based on the formation of a precipitate, a change in clarity, immiscibility, or a rapid loss of potency of acetylcysteine or the active ingredient of the PRODUCT AND/OR AGENT in the admixture.
The rating, Compatible, means that there was no significant physical change in the admixture when compared with a control solution of the PRODUCT AND/OR AGENT, and that there was no predicted chemical incompatibility. All of the admixtures have been tested for short-term chemical compatibility by assaying for the concentration of acetylcysteine after mixing.
2. The active ingredient in the PRODUCT AND/OR AGENT was also assayed after mixing. Some of the admixtures developed minor physical changes which were considered to be insufficient to rate the admixture Incompatible. These are listed in footnotes 3, 4, and 5.
3. A strong odor developed after storage for 24 hours at room temperature.
4. The admixture was a slightly darker shade of yellow than a control solution of the PRODUCT AND/OR AGENT.
5. A light tan color developed after storage for 24 hours at room temperature.
6. Entries are final concentrations. Values in parentheses relate volumes of acetylcysteine solutions to volume of test solutions.

CLINICAL PHARMACOLOGY

(Antidotal) Acetaminophen is rapidly absorbed from the upper gastrointestinal tract with peak plasma levels occurring between 30 and 60 minutes after therapeutic doses and usually within 4 hours following an overdose. The parent compound, which is nontoxic, is extensively metabolized in the liver to form principally the sulfate and glucuronide conjugates which are also nontoxic and are rapidly excreted in the urine. A small fraction of an ingested dose is metabolized in the liver by the cytochrome P-450 mixed function oxidase enzyme system to form a reactive, potentially toxic, intermediate metabolite which preferentially conjugates with hepatic glutathione to form the nontoxic cysteine and mercapturic acid derivatives which are then excreted by the kidney. Therapeutic doses of acetaminophen do not saturate the glucuronide and sulfate conjugation pathways and do not result in the formation of sufficient reactive metabolite to deplete glutathione stores. However, following ingestion of a large overdose (150 mg/kg or greater) the glucuronide and sulfate conjugation pathways are saturated resulting in a larger fraction of the drug being metabolized via the P-450 pathway. The increased formation of reactive metabolite may deplete the hepatic stores of glutathione with subsequent binding of the metabolite to protein molecules within the hepatocyte resulting in cellular necrosis.

Acetylcysteine has been shown to reduce the extent of liver injury following acetaminophen overdose. Its effectiveness depends on early oral administration, with benefit seen principally in patients treated within 16 hours of the overdose. Acetylcysteine probably protects the liver by maintaining or restoring the glutathione levels, or by acting as an alternate substrate for conjugation with, and thus detoxification of, the reactive metabolite.

INDICATIONS AND USAGE

Acetylcysteine, administered orally, is indicated as an antidote to prevent or lessen hepatic injury which may occur following the ingestion of a potentially hepatotoxic quantity of acetaminophen.

It is essential to initiate treatment as soon as possible after the overdose and, in any case, within 24 hours of ingestion.

CONTRAINDICATIONS

There are no contraindications to oral administration of acetylcysteine in the treatment of acetaminophen overdose.

WARNINGS

Generalized urticaria has been observed rarely in patients receiving oral acetylcysteine for acetaminophen overdose. If this occurs or other allergic symptoms appear, treatment with acetylcysteine should be discontinued unless it is deemed essential and the allergic symptoms can be otherwise controlled.

If encephalopathy due to hepatic failure becomes evident, acetylcysteine treatment should be discontinued to avoid further administration of nitrogenous substances. There are no data indicating that acetylcysteine influences hepatic failure, but this remains a theoretical possibility.

PRECAUTIONS

Occasionally severe and persistent vomiting occurs as a symptom of acute acetaminophen overdose. Treatment with oral acetylcysteine may aggravate the vomiting. Patients at risk of gastric hemorrhage (eg, esophageal varices, peptic ulcers, etc.) should be evaluated concerning the risk of upper gastrointestinal hemorrhage versus the risk of developing hepatic toxicity, and treatment with acetylcysteine given accordingly.

Dilution of the acetylcysteine (see Preparation of Acetylcysteine for Oral Administration) minimizes the propensity of oral acetylcysteine to aggravate vomiting.

ADVERSE REACTIONS

Oral administration of acetylcysteine, especially in the large doses needed to treat acetaminophen overdose, may result in nausea, vomiting and other gastrointestinal symptoms. Rash with or without mild fever has been observed rarely.

DOSAGE AND ADMINISTRATION

General

Regardless of the quantity of acetaminophen reported to have been ingested, administer acetylcysteine immediately if 24 hours or less have elapsed from the reported time of ingestion of an overdose of acetaminophen. Do not await results of assays for acetaminophen level before initiating treatment with acetylcysteine. The following procedures are recommended:

1. The stomach should be emptied promptly by lavage or by inducing emesis with syrup of ipecac. Syrup of ipecac should be given in a dose of 15 mL for children up to age 12 and 30 mL for adolescents and adults followed immediately by drinking copious amounts of water. The dose should be repeated if emesis does not occur in 20 minutes.
2. In the case of a mixed drug overdose activated charcoal may be indicated. However, if activated charcoal has been administered, lavage before administering acetylcysteine treatment. Activated charcoal adsorbs acetylcysteine in vitro and may do so in patients and thereby may reduce its effectiveness.
3. Draw blood for predetoxification acetaminophen plasma assay and baseline SGOT, SGPT, bilirubin, prothrombin time, creatinine, BUN, blood sugar and electrolytes.
4. Administer the loading dose of acetylcysteine, 140 mg per kg of body weight. (Prepare acetylcysteine for oral administration as described in the Dosage Guide and Preparation table).
5. Determine subsequent action based on predetoxification plasma acetaminophen information. Choose ONE of the following four courses of therapy.
  1. Predetoxification plasma acetaminophen level is clearly in the toxic range (See Acetaminophen Assays - Interpretation and Methodology below):
    Administer a first maintenance dose (70 mg/kg acetylcysteine) 4 hours after the loading dose. The maintenance dose is then repeated at 4-hour intervals for a total of 17 doses. Monitor hepatic and renal function and electrolytes throughout the detoxification process.
  2. Predetoxification acetaminophen level could not be obtained
    Proceed as in A.
  3. Predetoxification acetaminophen level is clearly in the non-toxic range (beneath the dashed line on the nomogram) and you know that acetaminophen overdose occurred at least 4 hours before the predetoxification acetaminophen plasma assays
    Discontinue administration of acetylcysteine.
  4. Predetoxification acetaminophen level was in the non-toxic range, but time of ingestion was unknown or less than 4 hours
    Because the level of acetaminophen at the time of predetoxification assay may not be a peak value (peak may not be achieved before 4 hours post-ingestion), obtain a second plasma level in order to decide whether or not the full 17-dose detoxification treatment is necessary.
6. If the patient vomits an oral dose within 1 hour of administration, repeat that dose.
7. In the occasional instances where the patient is persistently unable to retain the orally administered acetylcysteine, the antidote may be administered by duodenal intubation.
8. Repeat SGOT, SGPT, bilirubin, prothrombin time, creatinine, BUN, blood sugar and electrolytes daily if the acetaminophen plasma level is in the potentially toxic range as discussed below.

Preparation of Acetylcysteine for Oral Administration

Oral administration requires dilution of the 20% solution with diet cola or other diet soft drinks, to a final concentration of 5% (see Dosage Guide and Preparation table). If administered via gastric tube or Miller-Abbott tube, water may be used as the diluent. The dilutions should be freshly prepared and utilized within one hour. Remaining undiluted solutions in opened vials can be stored in the refrigerator up to 96 hours.
ACETYLCYSTEINE IS NOT APPROVED FOR PARENTERAL INJECTION.

ACETAMINOPHEN ASSAYS - INTERPRETATION AND METHODOLOGY

The acute ingestion of acetaminophen in quantities of 150 mg/kg or greater may result in hepatic toxicity. However, the reported history of the quantity of a drug ingested as an overdose is often inaccurate and is not a reliable guide to therapy of the overdose. THEREFORE, PLASMA OR SERUM ACETAMINOPHEN CONCENTRATIONS, DETERMINED AS EARLY AS POSSIBLE, BUT NO SOONER THAN 4 HOURS FOLLOWING AN ACUTE OVERDOSE, ARE ESSENTIAL IN ASSESSING THE POTENTIAL RISK OF HEPATOTOXICITY. IF AN ASSAY FOR ACETAMINOPHEN CANNOT BE OBTAINED, IT IS NECESSARY TO ASSUME THAT THE OVERDOSE IS POTENTIALLY TOXIC.

INTERPRETATION OF ACETAMINOPHEN ASSAYS

1. When results of the plasma acetaminophen assay are available refer to the nomogram below to determine if plasma concentration is in the potentially toxic range. Values above the solid line connecting 200 mcg/mL at 4 hours with 50 mcg/mL at 12 hours are associated with a possibility of hepatic toxicity if an antidote is not administered. (Do not wait for assay results to begin acetylcysteine treatment.)
2. If the predetoxification plasma level is above the broken line continue with maintenance doses of acetylcysteine. It is better to err on the safe side and thus the broken line is placed 25% below the solid line which defines possible toxicity.
3. If the predetoxification plasma level is below the broken line described above, there is minimal risk of hepatic toxicity and acetylcysteine treatment can be discontinued.

ACETAMINOPHEN ASSAY METHODOLOGY

Assay procedures most suitable for determining acetaminophen concentrations utilize high pressure liquid chromatography (HPLC) or gas liquid chromatography (GLC). The assay should measure only parent acetaminophen and not conjugated. The assay procedures listed below fulfill this requirement:

SELECTED TECHNIQUES (non inclusive)

HPLC:

1. Blair D, Rumack, BH, Clin Chem, 1977; 23(4):743-745.
2. Howie D, Andriaenssens Pl, Prescott LF. J. Pharm Pharmacol, 1977; 29(4):235-237. GLC
3. Prescott LF. J. Pharm Pharmacol, 1971; 23(10):807-808. Colorimetric
4. Glynn JP. Kendal SE, Lancet 1975; 1(May 17):1147-1148.

Supportive Treatment of Acetaminophen Overdose

1. Maintain fluid and electrolyte balance based on clinical evaluation of state of hydration and serum electrolytes.
2. Treat as necessary for hypoglycemia.
3. Administer vitamin K1 if prothrombin time ratio exceeds 1.5 or fresh frozen plasma if the prothrombin time ratio exceeds 3.0.
4. Diuretics and forced diuresis should be avoided.

DOSAGE GUIDE AND PREPARATION

Doses in relation to body weight are:

Loading Dose of Acetylcysteine **
 |  | grams | mL of 20% | mL of | Total mL of
Body Weight |  | Acetylcysteine | Acetylcysteine | Diluent | 5% Solution
(kg) | (lb)
100-109 | 220-240 | 15 | 75 | 225 | 300
90-99 | 198-218 | 14 | 70 | 210 | 280
80-89 | 176-196 | 13 | 65 | 195 | 260
70-79 | 154-174 | 11 | 55 | 165 | 220
60-69 | 132-152 | 10 | 50 | 150 | 200
50-59 | 110-130 | 8 | 40 | 120 | 160
40-49 | 88-108 | 7 | 35 | 105 | 140
30-39 | 66-86 | 6 | 30 | 90 | 120
20-29 | 44-64 | 4 | 20 | 60 | 80
Maintenance Dose**
(kg) | (lb)
100-109 | 220-240 | 7.5 | 37 | 113 | 150
90-99 | 198-218 | 7 | 35 | 105 | 140
80-89 | 176-196 | 6.5 | 33 | 97 | 130
70-79 | 154-174 | 5.5 | 28 | 82 | 110
60-69 | 132-152 | 5 | 25 | 75 | 100
50-59 | 110-130 | 4 | 20 | 60 | 80
40-49 | 88-108 | 3.5 | 18 | 52 | 70
30-39 | 66-86 | 3 | 15 | 45 | 60
20-29 | 44-64 | 2 | 10 | 30 | 40
**If patient weighs less than 20 kg (usually patients younger than 6 years), calculate the dose of acetylcysteine. Each mL of 20% acetylcysteine solution contains 200 mg of acetylcysteine. The loading dose is 140 mg per kilogram of body weight. The maintenance dose is 70 mg/kg. Three (3) mL of diluent are added to each mL of 20% acetylcysteine solution. Do not decrease the proportion of diluent.

Estimating Potential for Hepatoxicity

The following nomogram has been developed to estimate the probability that plasma levels in relation to intervals post ingestion will result in hepatoxicity.

Plasma or Serum Acetaminophen Concentration v Time Post-acetaminophen Ingestion

HOW SUPPLIED

Acetylcysteine is available in rubber stoppered glass vials containing 4, 10, or 30 mL. The 20% solution may be diluted to a lesser concentration with either Sodium Chloride for Injection, Sodium Chloride for Inhalation, Sterile Water for Injection, or Sterile Water for Inhalation. The 10% solution may be used undiluted.

Acetylcysteine solution is sterile and can be used for inhalation (mucolytic agent) or oral administration (acetaminophen antidote). Acetylcysteine solution is not for parenteral injection. It is available as:

Acetylcysteine 20% solution (200 mg acetylcysteine per mL). Sterile, not for injection.

Overbagged with 5 x 4 mL vials in each bag, NDC 55154-5731-5

Acetylcysteine 10% solution (100 mg acetylcysteine per mL). Sterile, not for injection.

Overbagged with 5 x 4 mL vials in each bag, NDC 55154-5730-5

WARNING: These Unit Dose packages are not child resistant and are Intended for Institutional Use Only. Keep this and all drugs out of the reach of children.

STORAGE

Store unopened vials at 20°-25°C (68°-77°F); excursions permitted to 15°-30°C (59°-86°F) (see USP Controlled Room Temperature).

Acetylcysteine solution does not contain an antimicrobial agent, and care must be taken to minimize contamination of the sterile solution. Dilutions of acetylcysteine should be used freshly prepared and utilized within one hour. If only a portion of the solution in a vial is used, store the remaining undiluted portion in a refrigerator and use within 96 hours. A change in color may occur after opening. This does not change the efficacy of the drug.

REFERENCES

1. Bonanomi L, Gazzaniga A. Toxicological, pharmacokinetic and metabolic studies on acetylcysteine. Eur J Respir Dis, 1981; 61 (Suppl III): 45-51.
2. Am Rev Respir Dis, 1960; 82:627-639.

Rx Only

IN7504
Rev. 5/14
MG #11105

AMERICAN
REGENT, INC.
SHIRLEY, NY 11967

Distributed By:

Cardinal Health

Dublin, OH 43017

L35753390524

L35753540824

Package/Label Display Panel

NDC 55154-5730-5

ACETYLCYSTEINE SOLUTIONS, USP

10% (100 mg/mL)

5 x 4 mL VIALS

Package/Label Display Panel

NDC 55154-5731-5

ACETYLCYSTEINE SOLUTIONS, USP

20% (200 mg/mL)

5 x 4 mL VIALS